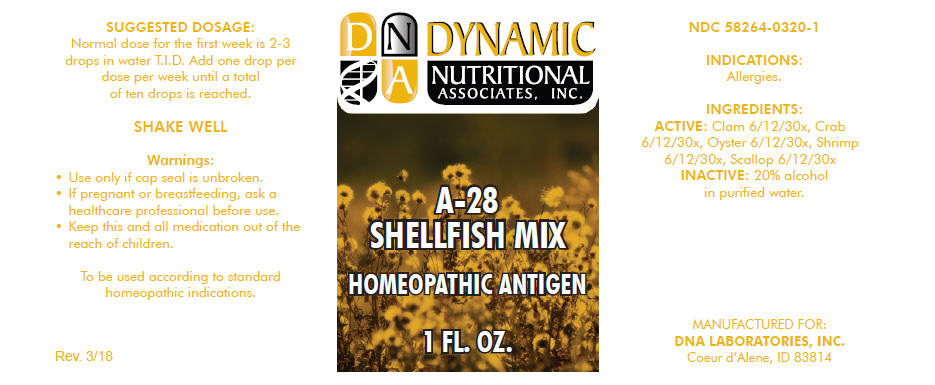 DRUG LABEL: A-28
NDC: 58264-0320 | Form: SOLUTION
Manufacturer: DNA Labs, Inc.
Category: homeopathic | Type: HUMAN OTC DRUG LABEL
Date: 20250109

ACTIVE INGREDIENTS: QUAHOG, UNSPECIFIED 30 [hp_X]/1 mL; BLUE CRAB 30 [hp_X]/1 mL; EDIBLE OYSTER 30 [hp_X]/1 mL; SHRIMP, UNSPECIFIED 30 [hp_X]/1 mL; SCALLOP, UNSPECIFIED 30 [hp_X]/1 mL
INACTIVE INGREDIENTS: ALCOHOL; WATER

A-28

NDC 58264-0320-1

INDICATIONS

PURPOSE

Allergies.

INGREDIENTS

ACTIVE

Clam 6/12/30x, Crab 6/12/30x, Oyster 6/12/30x, Shrimp 6/12/30x, Scallop 6/12/30x

INACTIVE

20% alcohol in purified water.

SUGGESTED DOSAGE

Normal dose for the first week is 2-3 drops in water T.I.D. Add one drop per dose per week until a total of ten drops is reached.

STORAGE AND HANDLING

SHAKE WELL

Warnings

- Use only if cap seal is unbroken.

PREGNANCY OR BREAST FEEDING

- If pregnant or breastfeeding, ask a healthcare professional before use.

KEEP OUT OF REACH OF CHILDREN

- Keep this and all medication out of the reach of children.

To be used according to standard homeopathic indications.

PRINCIPAL DISPLAY PANEL - 1 FL. OZ. Bottle Label

DYNAMIC
NUTRITIONAL
ASSOCIATES, INC.

A-28
SHELLFISH MIX

HOMEOPATHIC ANTIGEN

1 FL. OZ.